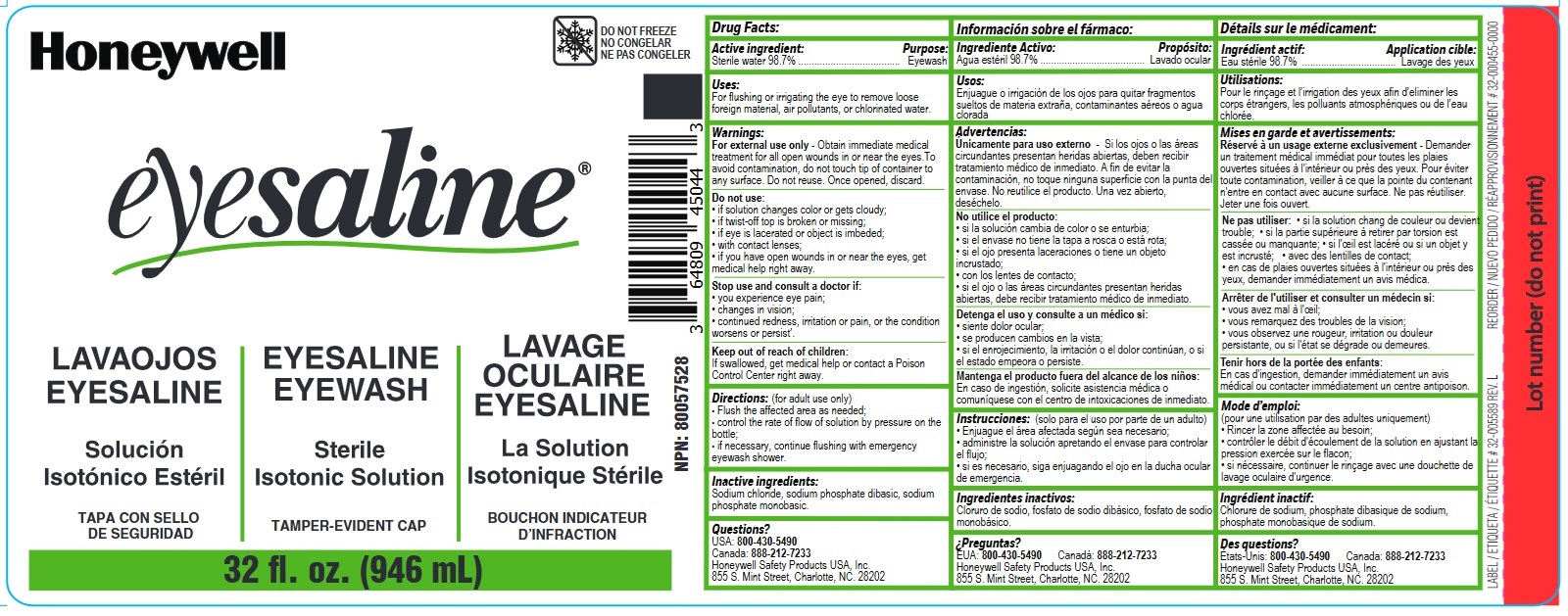 DRUG LABEL: Eyesaline Emergency Eyewash
NDC: 0498-2500 | Form: LIQUID
Manufacturer: Honeywell Safety Products USA, Inc.
Category: otc | Type: HUMAN OTC DRUG LABEL
Date: 20250514

ACTIVE INGREDIENTS: WATER 98.7 mL/100 mL
INACTIVE INGREDIENTS: SODIUM CHLORIDE; SODIUM PHOSPHATE, MONOBASIC, MONOHYDRATE; SODIUM PHOSPHATE, DIBASIC

Sterile Eyewash Eyesaline

ACTIVE INGREDIENT

Sterile water 98.7%

PURPOSE

Eyewash

INDICATIONS AND USAGE

For flushing the eye to remove loose foreign material, air pollutants or chlorinated water

WARNINGS

For external use only- Obtain immediate medical treatment for all open wounds in or near eyes. To avoid contamination, do not touch tip of container to any surface. Do not reuse. Once opened, discard.

DO NOT USE

if solution changes color or becomes cloudy
if twist-off top is broken or missing
if eye is lacerated or object is imbeded
with contact lenses
if you have open wounds in or near the eyes, get medical help right away.

STOP USE

You experience eye pain
Changes in vision
Continued redness, irritation or pain, or if the condition worsens or persist

KEEP OUT OF REACH OF CHILDREN

If swallowed, get medical help or contact a Poison Control Center right away.

DOSAGE AND ADMINISTRATION

Flush the affected area as needed.
Control the rate of flow of solution by pressure on the bottle.
If necessary, continue flushing with emergency eyewash shower.

INACTIVE INGREDIENT

Sodium chloride, sodium phosphate dibasic, sodium phosphate monobasic

QUESTIONS

USA: 800 430-5490
Canada: 888 212-7233
Honeywell Safety Products USA, 855 S. Mint Street, Charlotte, NC 28202